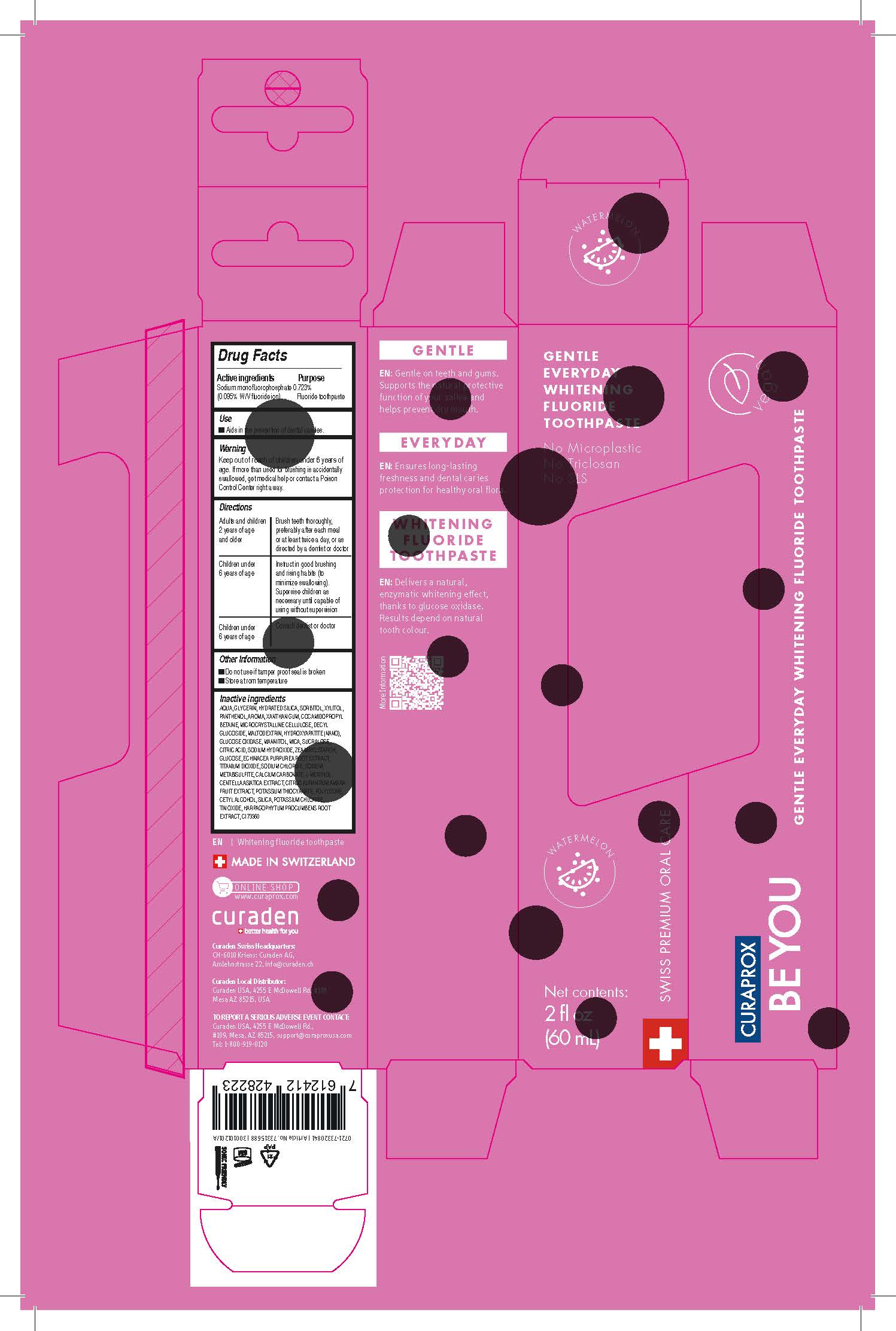 DRUG LABEL: BEYOU Pink
NDC: 71112-002 | Form: PASTE, DENTIFRICE
Manufacturer: Curaden AG
Category: otc | Type: HUMAN OTC DRUG LABEL
Date: 20220712

ACTIVE INGREDIENTS: SODIUM MONOFLUOROPHOSPHATE 0.095 g/100 mL
INACTIVE INGREDIENTS: WATER; POTASSIUM THIOCYANATE

Active Ingredient(s)

Sodium monofluorophosphate 0.723%
(0.095% W/V fluoride ion)

Purpose

Floride toothpaste

Use

Aids in the prevention of dental cavities.

Warnings

Keep out of reach of children under 6 years old. If more than used for brushing is accidentally swallowed, get medical help or contact a Poison Control Center right away.

Specific Warning for OTC

Keep out of reach of children under 6 years old. If more than used for brushing is accidentally swallowed, get medical help or contact a Poison Control Center right away.

Directions

Adults and children 2 years of age and older: Brush teeth thoroughly, preferably afler each meal or at least twice a day, or as directed by a dentist or doctor

Children under 6 years of age: Instructin good brushing and rising habits (to minimize swallowing). Supervise children as necessary until capable of using without supervision

Children under 6 years of age: Consult dentist or doctor

Other information

Do nont use if tamper proof seal is broken

Store at room temperature

Inactive ingredients

AQUA, GLYCERIN, HYDRATED SILICA, SORBITOL, XYLITOL, PANTHENOL, AROMA, XANTHAN GUM, COCAMIDOPROPYL BETAINE, MICRCX::RYSTALLINE CELlULOSE, DECYL GLUCOSIDE, MALTODEXTRIN, HYDROXYAPATITE (NANO), GLUCOSE OXIDASE, MANNITOL, MICA, SUCRALOSE, CITRIC ACID, SODIUM HYDROXIDE, ZEA MAYS STARCH, GLUCOSE, ECHINACEA PURPUREA ROOT EXTRACT, TITANIUM DIOXIDE, SODIUM CHLORIDE, SODIUM METABISULFITE, CALCIUM CARBONATE, L-MENTHOL, CENTELLA ASIATICA EXTRACT, CITRUS AURANTIUM AMARA FRUIT EXTRACT, POTASSIUM THIOCYANATE, POLYLYSINE, CETYLALCOHOL, SILICA, POTASSIUM CHLORIDE, TIN OXIDE, HARPAGOPHYTlJM PRCX::UMBENS ROOT EXTRACT, Cl 73360 (D&C Red 30)

Dose and Methods per Use

A pea-sized amount of toothpaste is enough. For the best whitening results: Do not rinse your mouth afterwards. Be gentle when brushing and use a toothbrush with soft, high-density bristles. Once a day, brush between your teeth with an interdental brush to keep your gums and teeth healthier, and your breath fresher.

Label Artwork

Drug Facts

Active Ingredients

Purpose

Use

Warning

Directions

Other Information

Inactive Ingredients

Curaden